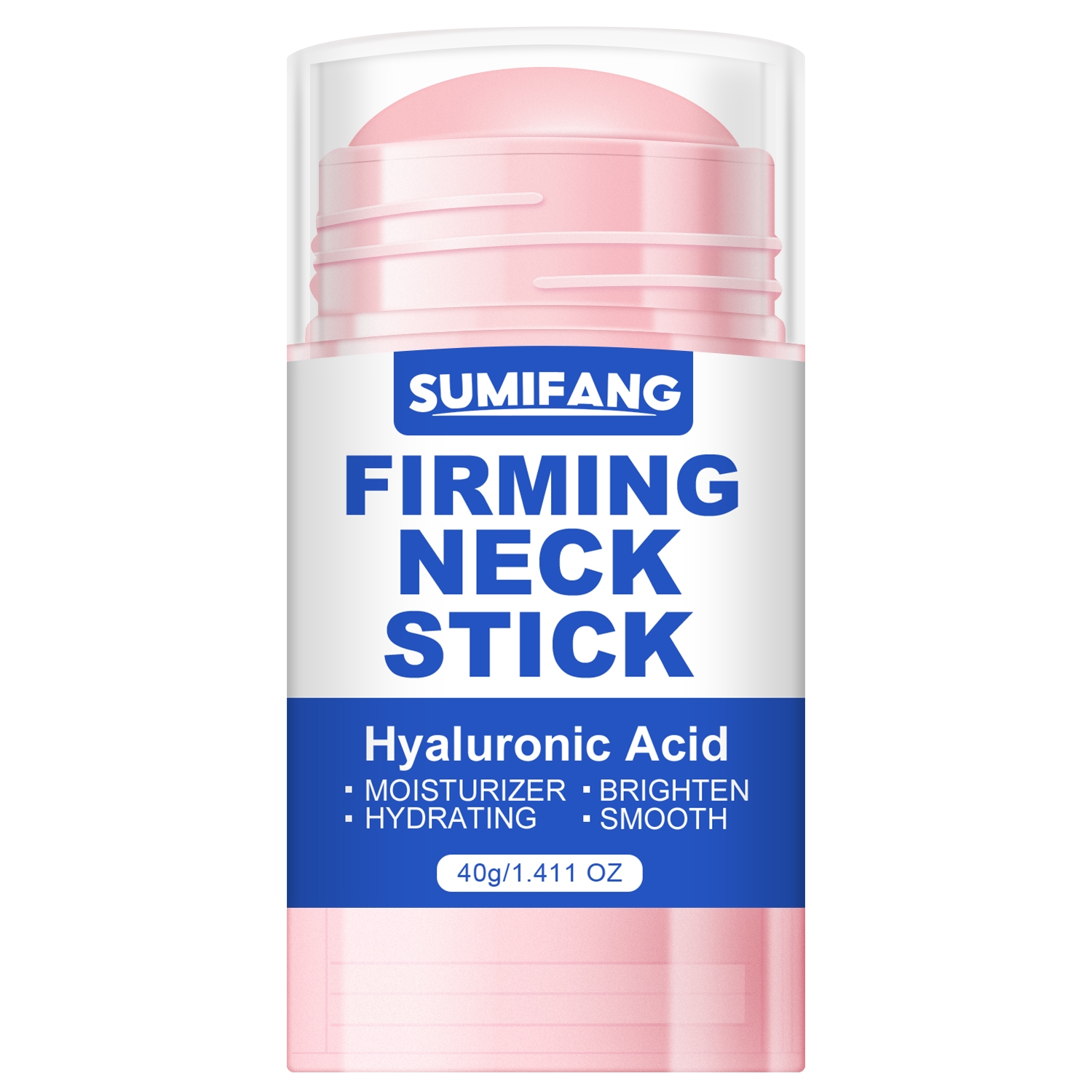 DRUG LABEL: FIRMING NECKSTICK
NDC: 84025-107 | Form: STICK
Manufacturer: Guangzhou Yanxi Biotechnology Co.. Ltd
Category: otc | Type: HUMAN OTC DRUG LABEL
Date: 20240801

ACTIVE INGREDIENTS: HYALURONIC ACID 5 mg/40 g; MINERAL OIL 3 mg/40 g
INACTIVE INGREDIENTS: WATER

DOSAGE AND ADMINISTRATION

stick for moisturizing and hydrating neck skin

WARNINGS

keep out of children

INACTIVE INGREDIENT

Aqua

INDICATIONS AND USAGE

For daily skin care

keep out of children

PURPOSE

Moisturizes and smoothes the neck